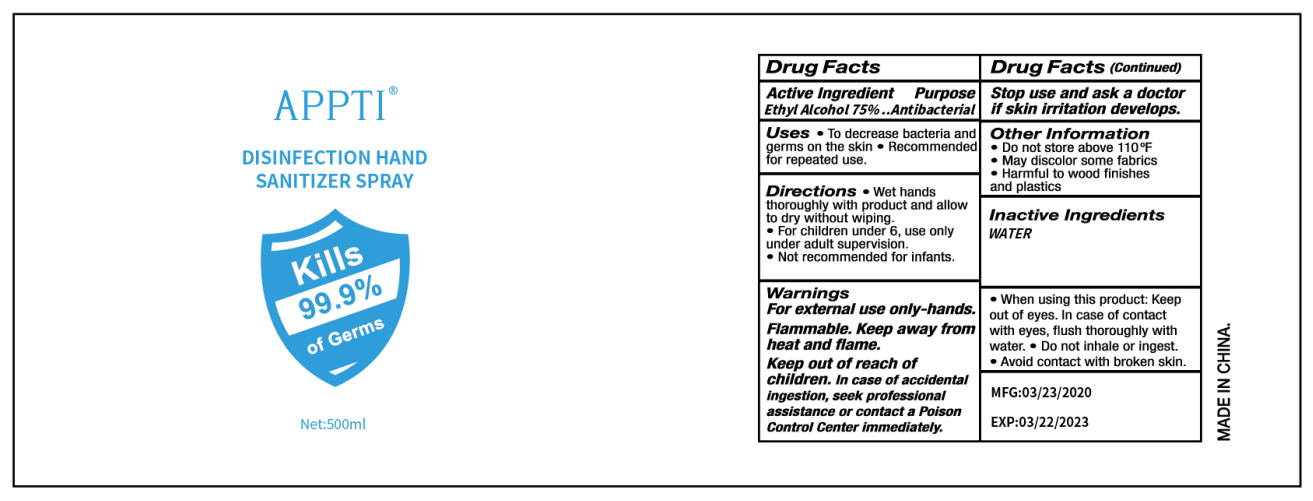 DRUG LABEL: Hand Sanitizer Liquid
NDC: 81309-006 | Form: LIQUID
Manufacturer: LYW BIOTECH CO LIMITED GUANGZHOU
Category: otc | Type: HUMAN OTC DRUG LABEL
Date: 20210221

ACTIVE INGREDIENTS: ALCOHOL 75 mL/100 mL
INACTIVE INGREDIENTS: WATER 25 mL/100 mL

Disinfection Hand Sanitizer Spray